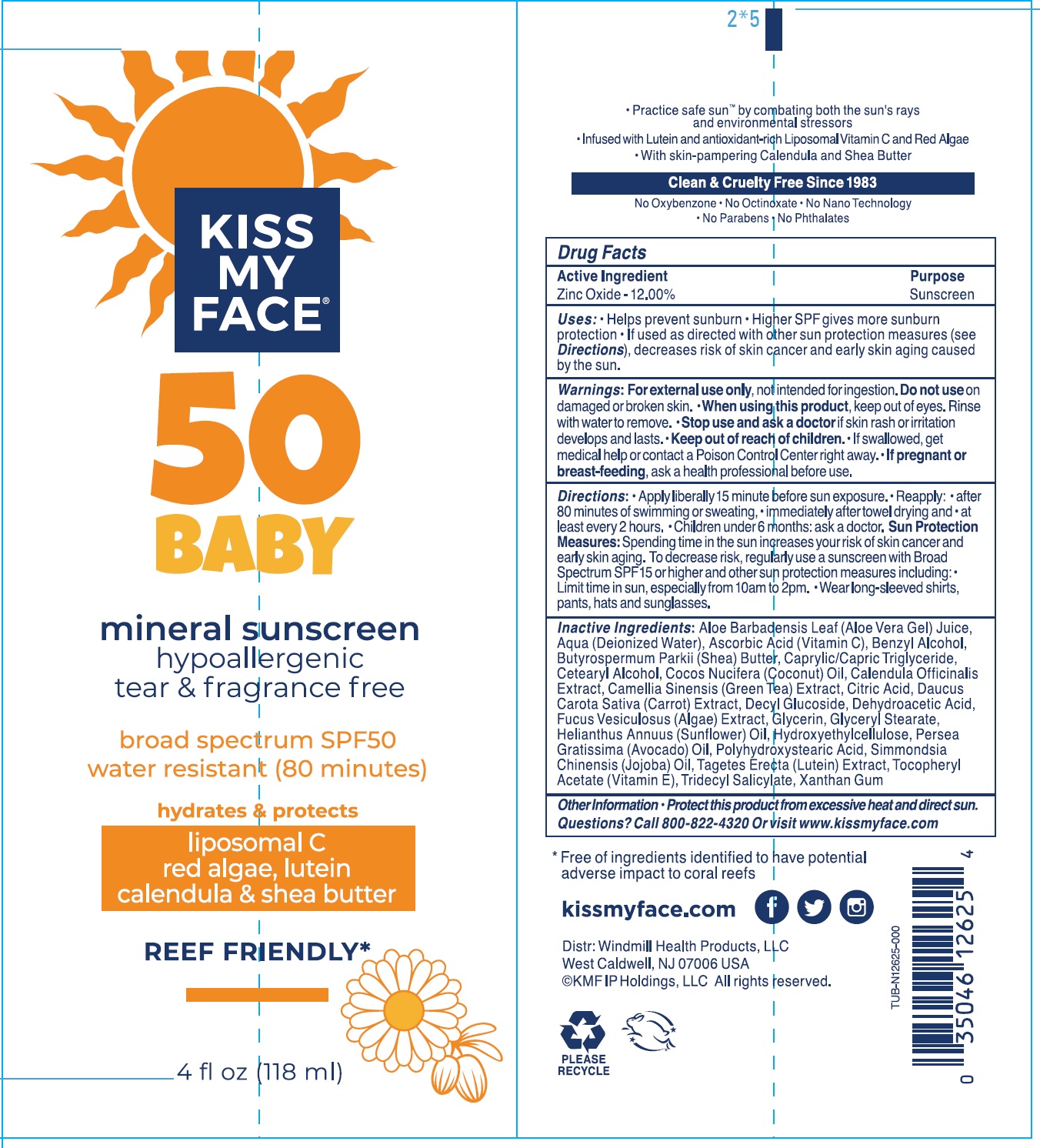 DRUG LABEL: KISS MY FACE SPF-50 Baby Mineral Sunscreen
NDC: 74154-317 | Form: CREAM
Manufacturer: WINDMILL HEALTH PRODUCTS LLC
Category: otc | Type: HUMAN OTC DRUG LABEL
Date: 20231111

ACTIVE INGREDIENTS: ZINC OXIDE 120 mg/1 mL
INACTIVE INGREDIENTS: ALOE VERA LEAF; WATER; ASCORBIC ACID; BENZYL ALCOHOL; SHEA BUTTER; MEDIUM-CHAIN TRIGLYCERIDES; CETOSTEARYL ALCOHOL; COCONUT OIL; CALENDULA OFFICINALIS FLOWER; GREEN TEA LEAF; CITRIC ACID MONOHYDRATE; CARROT; DECYL GLUCOSIDE; DEHYDROACETIC ACID; FUCUS VESICULOSUS; GLYCERIN; GLYCERYL MONOSTEARATE; HELIANTHUS ANNUUS FLOWERING TOP; HYDROXYETHYL CELLULOSE, UNSPECIFIED; AVOCADO OIL; JOJOBA OIL; .ALPHA.-TOCOPHEROL ACETATE; TRIDECYL SALICYLATE; XANTHAN GUM

KISS MY FACE SPF-50 Baby Mineral Sunscreen

Active Ingredient

Zinc Oxide - 12.00%

Purpose

Sunscreen

Uses:

- Helps prevent sunburn
- Higher SPF gives more sunburn protection
- If used as directed with other sun protection measures (see), decreases risk of skin cancer and early skin aging caused by the sun. Directions

Warnings:

not intended for ingestion. For external use only,

Do not use

on damaged or broken skin.

When using this product,

- keep out of eyes. Rinse with water to remove.

Stop use and ask a doctor if

- skin rash or irritation develops and lasts.

Keep out of reach of children.

- If swallowed, get medical help or contact Poison Control Center right away..

If pregnant or breast-feeding,

- ask a health professional before use.

Directions:

- Apply liberally 15 minute before sun exposure.
- Reapply:
- after 80 minutes of swimming or sweating,
- immediately after towel drying and
- at least every 2 hours.
- Children under 6 months: ask a doctor.
- Spending time in the sun increases your risk of skin cancer and early skin aging. To decrease risk, regularly use sunscreen with Broad Spectrum SPF 15 or higher and other sun protection measures including: Sun Protection Measures:
- Limit time in sun, especially from 10am to 2pm.
- Wear long-sleeved shirts, pants, hats and sunglasses.

Inactive Ingredients:

Aloe Barbadensis Leaf (Aloe Vera Gel) Juice, Aqua (Deionized Water), Ascorbic Acid (Vitamin C), Benzyl Alcohol, Butyrospermum Parkii (Shea) Butter, Caprylic/Capric Triglyceride, Cetearyl Alcohol, Cocos Nucifera (Coconut) Oil, Calendula Officinalis Extract, Camellia Sinensis (Green Tea) Extarct, Citric Acid, Daucus Carota Sative (Carrot) Extract, Decyl Glucoside, Dehydroacetic Acid, Fucus Vesiculosus (Algae) Extract, Glycerin, Glyceryl Stearate, Helianthus Annuus (Sunflower) Oil, Hydroxyethylcellulose, Persea Gratissima (Avocado) Oil, Polyhydroxystearic Acid, Simmondsia Chinensis (Jojoba) Oil, Tagetes Erecta(Lutin) Extract, Tocopheryl Acetate (Vitamin E), Tridecyl Salicylate, Xanthan Gum

Other Information

- Protect this product from excessive heat and direct sun.

Questions?

Call 800-822-4320 or visit www.kissmyface.com